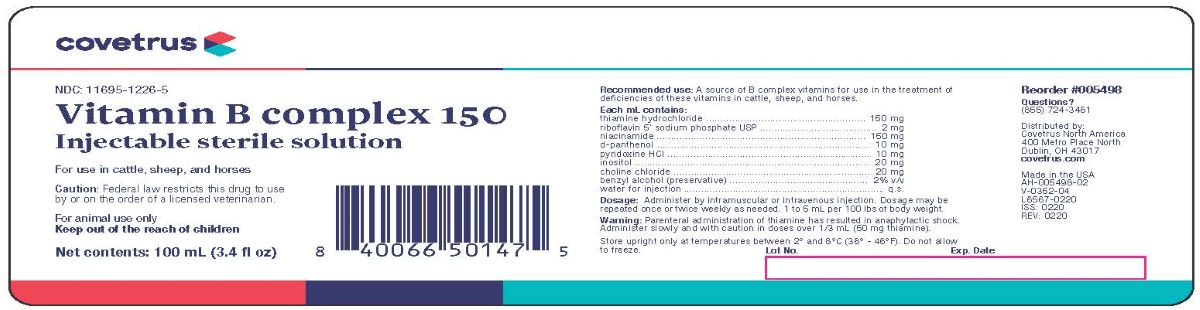 DRUG LABEL: Vitamin B Complex 150
NDC: 11695-1226 | Form: INJECTION
Manufacturer: Covetrus North America
Category: animal | Type: PRESCRIPTION ANIMAL DRUG LABEL
Date: 20231213

ACTIVE INGREDIENTS: THIAMINE HYDROCHLORIDE 150 mg/1 mL; RIBOFLAVIN 5'-PHOSPHATE SODIUM 2 mg/1 mL; NIACINAMIDE 150 mg/1 mL; PANTHENOL 10 mg/1 mL; PYRIDOXINE HYDROCHLORIDE 10 mg/1 mL; INOSITOL 20 mg/1 mL; CHOLINE CHLORIDE 20 mg/1 mL
INACTIVE INGREDIENTS: BENZYL ALCOHOL .02 mL/1 mL; WATER

Vitamin B Complex 150
Injectable Sterile Solution

Recommended Use:

A source of B complex vitamins for use in the treatment of deficiencies of these vitamins in cattle, sheep and horses.

Each mL Contains:

Thiamine Hydrochloride..................................................150 mg

Riboflavin 5' Sodium Phosphate USP....................................2 mg

Niacinamide..................................................................150 mg

d-Panthenol....................................................................10 mg

Pyridoxine HCL................................................................10 mg

Inositol..........................................................................20 mg

Choline Chloride..............................................................20 mg

Benzyl Alcohol (preservative)...........................................2% v/v

Water for Injection...............................................................q.s.

Dosage:

Administer by intramuscular or intravenous injection. Dosage may be repeated once or twice weekly as needed. 1 to 5
mL per 100 lbs of body weight.

Warning:

Parenteral administration of thiamine has resulted in anaphylactic shock. Administer slowly and with caution in doses
over 1/3 mL (50 mg Thiamine).

STORAGE AND HANDLING

Store upright only at temperatures between 2° and 8°C (36° - 46°F). Do not allow to freeze.

Questions?

(855) 724-3461

Distributed by:

Covetrus North America
400 Metro Place North
Dublin, OH 43017
covetrus.com

Made in USA

AH-005498-02
V-0352-04

L6567-0220

ISS:0220

Rev: 0220

Lot No.:

Exp. Date

Principal Display Panel

NDC: 11695-1226-5

Vitamin B complex 150
Injectable sterile solution

For use in cattle, sheep, and horses

Caution: Federal law restricts this drug to use by or on the order of a licensed veterinarian

FOR ANIMAL USE ONLY

KEEP OUT OF THE REACH OF CHILDREN

100 mL (3.4 fl oz)